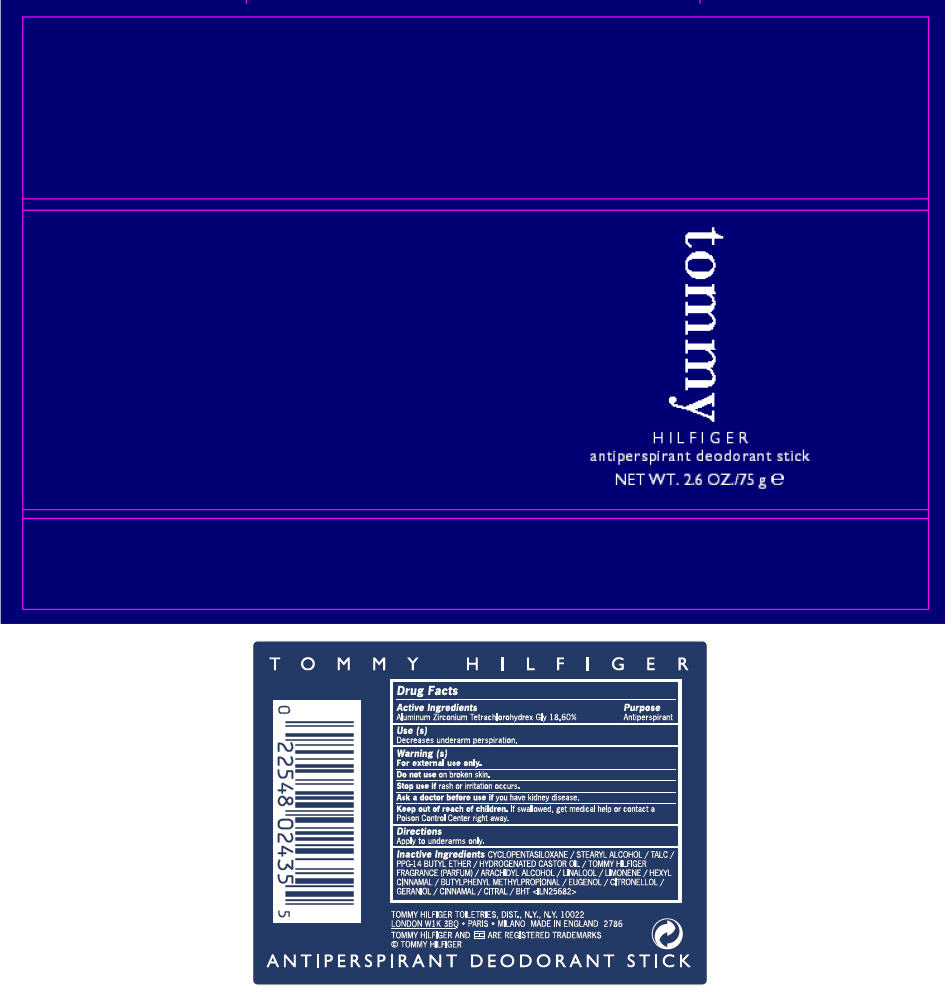 DRUG LABEL: TOMMY HILFIGER 
NDC: 64268-694 | Form: STICK
Manufacturer: TOMMY HILFIGER TOILETRIES
Category: otc | Type: HUMAN OTC DRUG LABEL
Date: 20210708

ACTIVE INGREDIENTS: ALUMINUM ZIRCONIUM TETRACHLOROHYDREX GLY 18.6 g/100 g
INACTIVE INGREDIENTS: CYCLOMETHICONE 5; STEARYL ALCOHOL; TALC; PPG-14 BUTYL ETHER; HYDROGENATED CASTOR OIL; ARACHIDYL ALCOHOL; LINALOOL, (+/-)-; .ALPHA.-HEXYLCINNAMALDEHYDE; BUTYLPHENYL METHYLPROPIONAL; EUGENOL; .BETA.-CITRONELLOL, (R)-; GERANIOL; CINNAMALDEHYDE; CITRAL; BUTYLATED HYDROXYTOLUENE

Tommy Hilfiger Antiperspirant Deodorant Stick

Drug Facts

Active Ingredients

Aluminum Zirconium Tetrachlorohydrex Gly 18.60%

Purpose

Antiperspirant

Use (s)

Decreases underarm perspiration.

Warning (s)

For external use only.

Do not use on broken skin.

Stop use if rash or irritation occurs.

Ask a doctor before use if you have kidney disease.

Keep out of reach of children. If swallowed, get medical help or contact a Poison Control Center right away.

Directions

Apply to underarms only.

Inactive Ingredients

CYCLOPENTASILOXANE / STEARYL ALCOHOL / TALC / PPG-14 BUTYL ETHER / HYDROGENATED CASTOR OIL / TOMMY HILFIGER FRAGRANCE (PARFUM) / ARACHIDYL ALCOHOL / LINALOOL / LIMONENE / HEXYL CINNAMAL / BUTYLPHENYL METHYLPROPIONAL / EUGENOL / CITRONELLOL / GERANIOL / CINNAMAL / CITRAL / BHT <ILN25682>

PRINCIPAL DISPLAY PANEL - 75 g Canister Label

tommy

HILFIGER
antiperspirant deodorant stick
NET WT. 2.6 OZ./75 g e